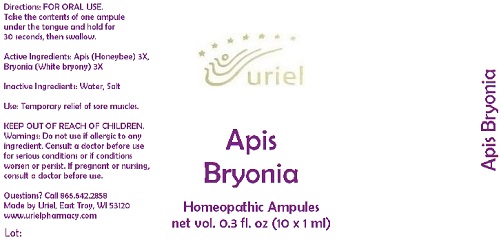 DRUG LABEL: Apis Bryonia
NDC: 48951-1050 | Form: LIQUID
Manufacturer: Uriel Pharmacy Inc.
Category: homeopathic | Type: HUMAN OTC DRUG LABEL
Date: 20170726

ACTIVE INGREDIENTS: APIS MELLIFERA 3 [hp_X]/1 mL; BRYONIA ALBA ROOT 3 [hp_X]/1 mL
INACTIVE INGREDIENTS: WATER; SODIUM CHLORIDE

Apis Bryonia

INDICATIONS AND USAGE

Directions: FOR ORAL USE.

DOSAGE AND ADMINISTRATION

Take the contents of one ampule under the tongue and hold for 30 seconds, then swallow.

ACTIVE INGREDIENT

Active Ingredients: Apis (Honeybee) 3X, Bryonia (White bryony) 3X

Inactive Ingredients: Water, Salt

PURPOSE

Use: Temporary relief of sore muscles.

KEEP OUT OF REACH OF CHILDREN.

WARNINGS

Warnings: Do not use if allergic to any ingredient. Consult a doctor before use for serious conditions or if conditions worsen or persist. If pregnant or nursing, consult a doctor before use.

QUESTIONS

Questions? Call 866.642.2858 Made by Uriel, East Troy, WI 53120 www.urielpharmacy.com